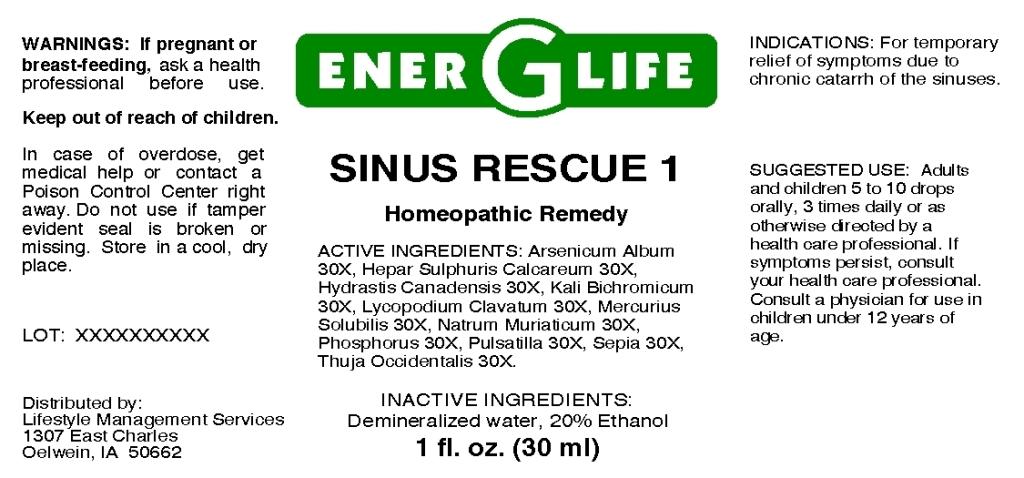 DRUG LABEL: Sinus Rescue
NDC: 57520-0654 | Form: LIQUID
Manufacturer: Apotheca Company
Category: homeopathic | Type: HUMAN OTC DRUG LABEL
Date: 20110331

ACTIVE INGREDIENTS: ARSENIC TRIOXIDE 30 [hp_X]/1 mL; CALCIUM SULFIDE 30 [hp_X]/1 mL; GOLDENSEAL 30 [hp_X]/1 mL; POTASSIUM DICHROMATE 30 [hp_X]/1 mL; LYCOPODIUM CLAVATUM SPORE 30 [hp_X]/1 mL; MERCURIUS SOLUBILIS 30 [hp_X]/1 mL; SODIUM CHLORIDE 30 [hp_X]/1 mL; PHOSPHORUS 30 [hp_X]/1 mL; PULSATILLA VULGARIS 30 [hp_X]/1 mL; SEPIA OFFICINALIS JUICE 30 [hp_X]/1 mL; THUJA OCCIDENTALIS LEAFY TWIG 30 [hp_X]/1 mL
INACTIVE INGREDIENTS: WATER; ALCOHOL

Sinus Rescue 1

ACTIVE INGREDIENT

ACTIVE INGREDIENTS: Arsenicum album 30X, Hepar sulphuris calcareum 30X, Hydrastis canadensis 30X, Kali bichromicum 30X, Lycopodium clavatum 30X, Mercurius solubilis 30X, Natrum muriaticum 30X, Phosphorus 30X, Pulsatilla 30X, Sepia 30X, Thuja occidentalis 30X.

PURPOSE

INDICATIONS: For temporary relief of symptoms due to chronic catarrh of the sinuses.

WARNINGS

WARNINGS: If pregnant or breast-feeding, ask a health professional before use.

Keep out of reach of children. In case of overdose, get medical help or contact a Poison Control Center right away.

Do not use if tamper evident seal if broken or missing. Store in a cool, dry place.

DOSAGE AND ADMINISTRATION

SUGGESTED USE: Adults and children 5 to 10 drops orally, 3 times daily or as otherwise directed by a health care professional. If symptoms persist, consult your health care professional. Consult a physician for use in children under 12 years of age.

INACTIVE INGREDIENTS: Demineralized water, 20% Ethanol.

KEEP OUT OF REACH OF CHILDREN. In case of overdose, get medical help or contact a Poison Control Center right away.

INDICATIONS AND USAGE

INDICATIONS: For temporary relief of symptoms due to chronic catarrh of the sinuses.

QUESTIONS

Distributed by:

Lifestyle Management Services

1307 East Charles

Oelwein, IA 50662

PACKAGE LABEL

ENER G LIFE

SINUS RESCUE 1

Homeopathic Remedy

1 fl. oz. (30 ml)